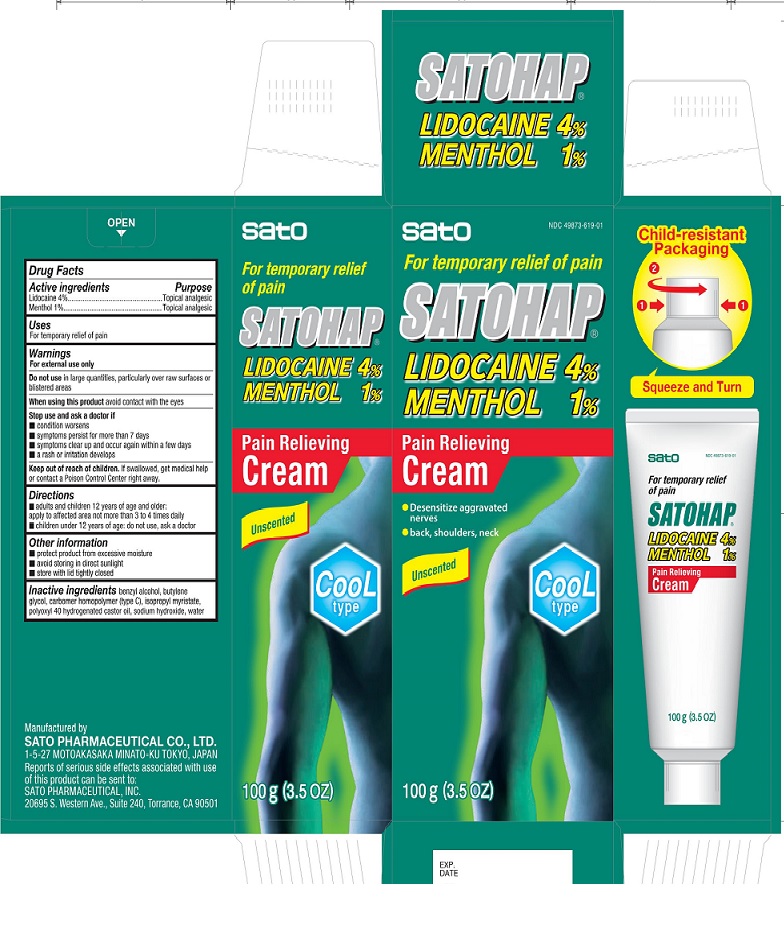 DRUG LABEL: Satohap Lidocaine 4% Menthol 1% Pain Relieving Cream
NDC: 49873-619 | Form: CREAM
Manufacturer: Sato Pharmaceutical Co., Ltd.
Category: otc | Type: HUMAN OTC DRUG LABEL
Date: 20241230

ACTIVE INGREDIENTS: LIDOCAINE 4 g/100 g; LEVOMENTHOL 1 g/100 g
INACTIVE INGREDIENTS: BENZYL ALCOHOL; BUTYLENE GLYCOL; CARBOMER HOMOPOLYMER TYPE C; ISOPROPYL MYRISTATE; POLYOXYL 40 HYDROGENATED CASTOR OIL; SODIUM HYDROXIDE; WATER

Satohap Lidocaine 4% Menthol 1% Cream

Active ingredients

Lidocaine 4%

Menthol 1%

Purpose

Lidocaine Topical analgesic

Menthol Topical analgesic

Uses

For temporary relief of pain

Warnings

For external use only

Do not use in large quantities, particularly over raw surfaces or blistered areas

When using this product avoid contact with the eyes

Stop use and ask a doctor if

- condition worsens
- symptoms persist for more than 7 days
- symptoms clear up and occur again within a few days
- a rash or irritation develops

Keep out of reach of children. If swallowed, get medical help or contact a Poison Control Center right away.

Directions

- adults and children 12 years of age and older: apply to affected area not more than 3 to 4 times dailly
- children under 12 years of age: do not use, ask a doctor

Other information

- protect product from excessive moisture
- avoid storing in direct sunlight
- store with lid tightly closed

INACTIVE INGREDIENT

Inactive ingredients benzyl alcohol, butylene glycol, carbomer homopolymer (type C), isopropyl myristate, polyoxyl 40 hydrogenated castor oil, sodium hydroxide, water